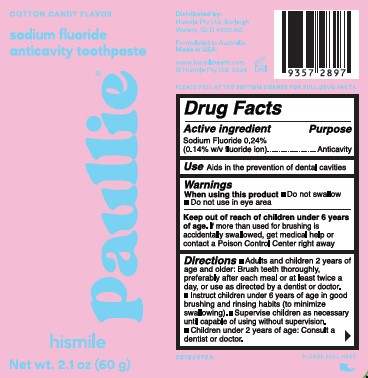 DRUG LABEL: HISMILE
NDC: 44038-0323 | Form: GEL
Manufacturer: Accupac LLC
Category: otc | Type: HUMAN OTC DRUG LABEL
Date: 20240918

ACTIVE INGREDIENTS: SODIUM FLUORIDE 0.243 g/100 g
INACTIVE INGREDIENTS: GLYCERIN; D&C RED NO. 33; WATER; XANTHAN GUM; LAURYL GLUCOSIDE; SODIUM GLUCONATE; HYDRATED SILICA; 1,2-HEXANEDIOL; ZINC LACTATE; METHYL DIISOPROPYL PROPIONAMIDE; SUCRALOSE; SODIUM LAUROYL SARCOSINATE; CARBOXYMETHYLCELLULOSE SODIUM, UNSPECIFIED FORM; SODIUM PHOSPHATE; XYLITOL; SORBITOL; POTASSIUM PYROPHOSPHATE

Active ingredient

Sodium Fluoride 0.243%

(0.14 w/v fluoride ion)

Purpose

Anticavity

Use

Aids in the prevention of dental cavities.

Warnings

Keep out of reach of children under 6 years of age

If more than used for brushing is accidentally swallowed, get medical help or contact a Poison Control Center right away.

When using this product

Do not swallow

Do not use in eye area

Directions

Adults and children 2 years of age and older: Brush teeth thoroughly, preferrably after each meal or at least twice a day, or use as directed by a dentist or doctor.

Instruct children under 6 years of age in good brushing and rinsing habtis (to minimize swallowing).

Supervise children as necessary until capable of using without supervision.

Children under 2 years of age: Consult a dentist or doctor.

Inactive Ingredients

Water

Sorbitol

Glycerin

Hydrated Silica

Xylitol

Sodium Phosphate

Xanthan Gum

Sodium Lauroyl Sarcosinate

Tetrapotassium Pyrophosphate

Methyl Diisopropyl Propionamide

Sodium Gluconate

Zinc Lactate

D&C Red No. 33

Label

Cotton Candy Label.jpg